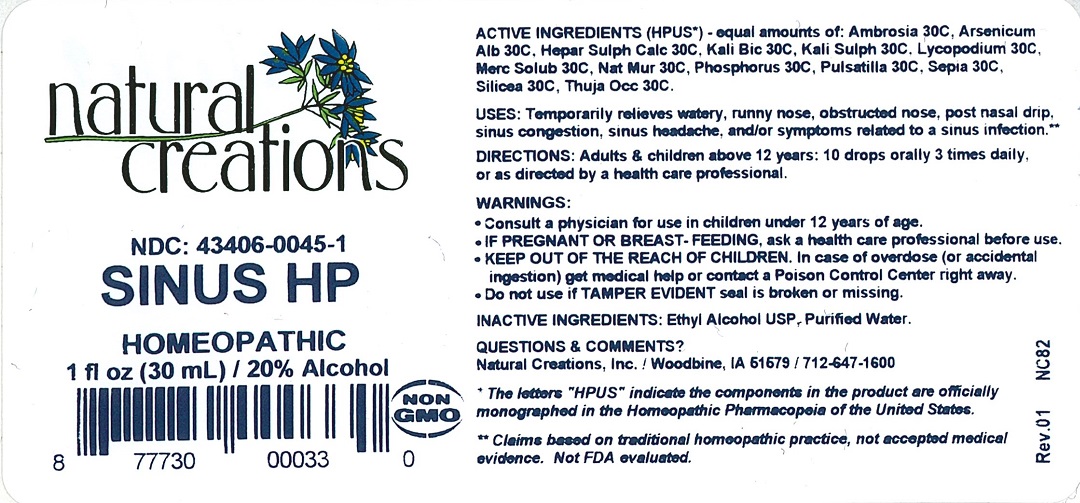 DRUG LABEL: SINUS HP
NDC: 43406-0045 | Form: LIQUID
Manufacturer: Natural Creations, Inc.
Category: homeopathic | Type: HUMAN OTC DRUG LABEL
Date: 20251216

ACTIVE INGREDIENTS: AMBROSIA ARTEMISIIFOLIA 30 [hp_C]/1 mL; ARSENIC TRIOXIDE 30 [hp_C]/1 mL; CALCIUM SULFIDE 30 [hp_C]/1 mL; POTASSIUM DICHROMATE 30 [hp_C]/1 mL; POTASSIUM SULFATE 30 [hp_C]/1 mL; LYCOPODIUM CLAVATUM SPORE 30 [hp_C]/1 mL; MERCURIUS SOLUBILIS 30 [hp_C]/1 mL; SODIUM CHLORIDE 30 [hp_C]/1 mL; PHOSPHORUS 30 [hp_C]/1 mL; PULSATILLA VULGARIS 30 [hp_C]/1 mL; SEPIA OFFICINALIS JUICE 30 [hp_C]/1 mL; SILICON DIOXIDE 30 [hp_C]/1 mL; THUJA OCCIDENTALIS LEAFY TWIG 30 [hp_C]/1 mL
INACTIVE INGREDIENTS: WATER; ALCOHOL

SINUS HP

ACTIVE INGREDIENT

ACTIVE INGREDIENTS (HPUS*) equal amounts of: Ambrosia 30C, Arsenicum Album 30C, Hepar Sulphuris Calcareum 30C, Kali Bichromicum 30C, Kali Sulphuricum 30C, Lycopodium Clavatum 30C, Mercurius Solubilis 30C, Natrum Muriaticum 30C, Phosphorus 30C, Pulsatilla 30C, Sepia 30C, Silicea 30C, Thuja Occidentalis 30C.

INDICATIONS AND USAGE

USES: Temporarily relieves watery, runny nose, obstructed nose, post nasal drip, sinus congestion, sinus headache, and/or symptoms related to a sinus infection.**

WARNING:

* Consult a physician for use in children under 12 years of age.

*IF PREGNANT OR BREAST-FEEDING, ask a health care professional before use.

* KEEP OUT OF THE REACH OF CHILDREN. In case of overdose (or accidental ingestion) get medical help or contact a Poison Control Center right away.

* Do not use if TAMPER EVIDENT seal is broken or missing.

DOSAGE AND ADMINISTRATION

DIRECTIONS: Adults and children above 12 years: 10 drops orally 3 times daily, or as directed by a health care professional.

REFERENCES

*The letters "HPUS" indicate the components in the product are officially monographed in the Homeopathic Pharmacopeia of the United States.

**Claims based on traditional homeopathic practice, not accepted medical evidence. Not FDA evaluated.

INACTIVE INGREDIENTS: Ethyl Alcohol USP, Purified Water.

QUESTIONS AND COMMENTS?

Natural Creations, Inc. / Woodbine, IA 51579 / 712-647-1600

PURPOSE

USES: Temporarily relieves watery, runny nose, obstructed nose, post nasal drip, sinus congestion, sinus headache, and/or symptoms related to a sinus infection.**

KEEP OUT OF REACH OF CHILDREN

KEEP OUT OF THE REACH OF CHILDREN. In case of overdose (or accidental ingestion) get medical help or contact a Poison Control Center.

PACKAGE LABEL

NDC: 43406-0045-1

SINUS HP

HOMEOPATHIC

1 fl oz (30 mL) / 20% Alcohol

UPC: 877730000330